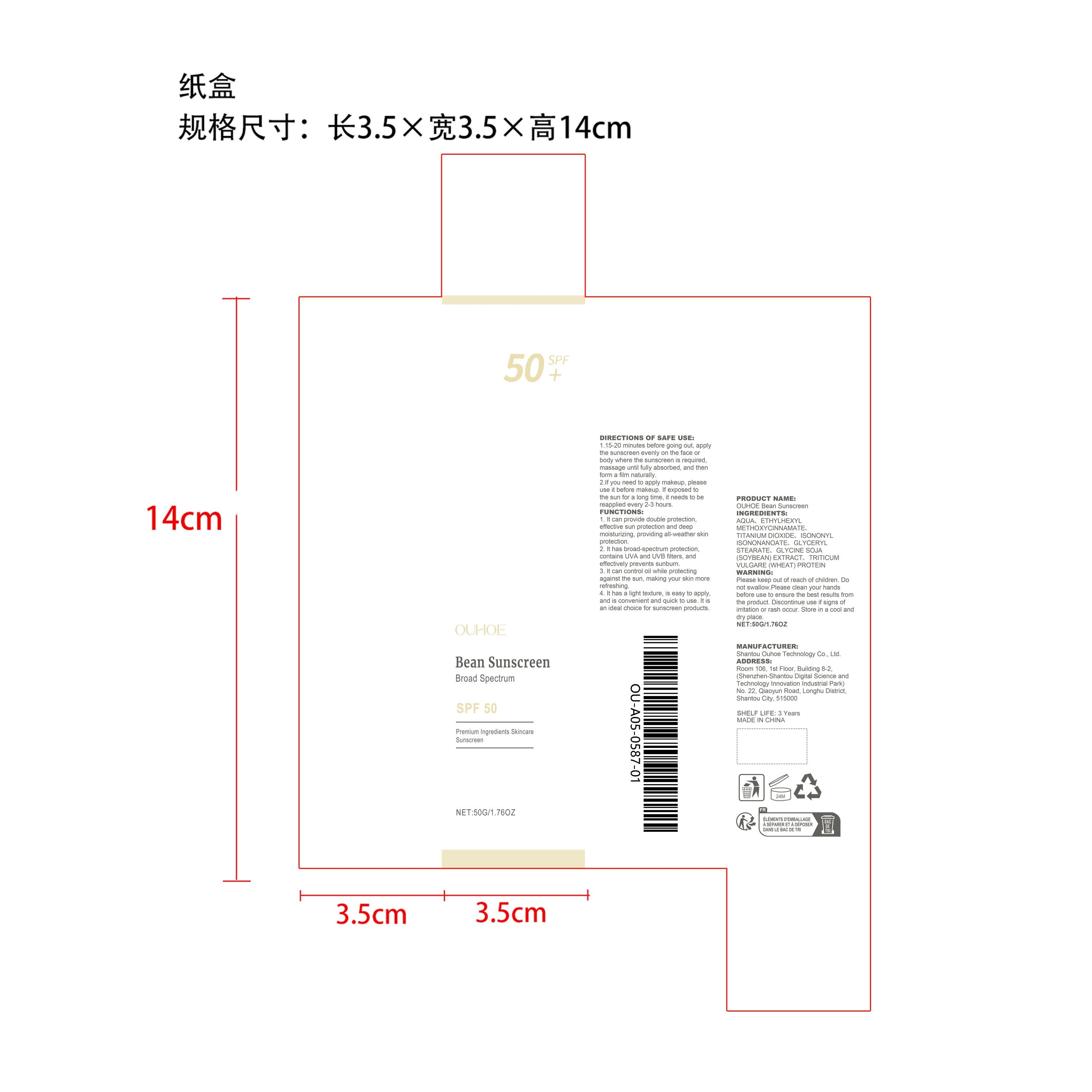 DRUG LABEL: OUHOE Bean Sunscreen
NDC: 85163-018 | Form: CREAM
Manufacturer: Shantou Ouhoe Technology Co., Ltd.
Category: otc | Type: HUMAN OTC DRUG LABEL
Date: 20251226

ACTIVE INGREDIENTS: TRITICUM VULGARE (WHEAT) GERM OIL 0.05 mg/50 mg; GLYCINE SOJA (SOYBEAN) OIL UNSAPONIFIABLES 0.05 mg/50 mg
INACTIVE INGREDIENTS: TITANIUM DIOXIDE 2.5 mg/50 mg; ETHYLHEXYL METHOXYCINNAMATE 2.5 mg/50 mg; ISONONYL ISONONANOATE 2 mg/50 mg; GLYCERYL STEARATE 1 mg/50 mg; AQUA 41.9 mg/50 mg

ACTIVE INGREDIENT

GLYCINE SOJA (SOYBEAN) EXTRACT、TRITICUM VULGARE (WHEAT) PROTEIN

PURPOSE

1. It can provide double protection, effective sun protection and deep moisturizing, providing all-weather skin protection.

2. It has broad-spectrum protection, contains UVA and UVB filters, and effectively prevents sunburn.

3. It can control oil while protecting against the sun, making your skin more refreshing.

4. It has a light texture, is easy to apply, and is convenient and quick to use. It is an ideal choice for sunscreen products.

WHEN USING

1.15-20 minutes before going out, apply the sunscreen evenly on the face or body where the sunscreen is required, massage until fully absorbed, and then form a film naturally.
2.If you need to apply makeup, please use it before makeup. If exposed to the sun for a long time, it needs to be reapplied every 2-3 hours.

WARNINGS

Please keep out of reach of children. Do not swallow.Please clean your hands before use to ensure the best results from the product. Discontinue use if signs of irritation or rash occur. Store in a cool and dry place.

DO NOT USE

Discontinue use if signs of irritation or rash occur.

STOP USE

Discontinue use if signs of irritation or rash occur.

KEEP OUT OF REACH OF CHILDREN

Please keep out of reach of children. Do not swallow.

STORAGE AND HANDLING

Store in a cool and dry place.

INACTIVE INGREDIENT

AQUA、ETHYLHEXYL METHOXYCINNAMATE、TITANIUM DIOXIDE、ISONONYL ISONONANOATE、GLYCERYL STEARATE

INDICATIONS AND USAGE

1.15-20 minutes before going out, apply the sunscreen evenly on the face or body where the sunscreen is required, massage until fully absorbed, and then form a film naturally.
2.If you need to apply makeup, please use it before makeup. If exposed to the sun for a long time, it needs to be reapplied every 2-3 hours.

DOSAGE AND ADMINISTRATION

1.15-20 minutes before going out, apply the sunscreen evenly on the face or body where the sunscreen is required, massage until fully absorbed, and then form a film naturally.
2.If you need to apply makeup, please use it before makeup. If exposed to the sun for a long time, it needs to be reapplied every 2-3 hours.